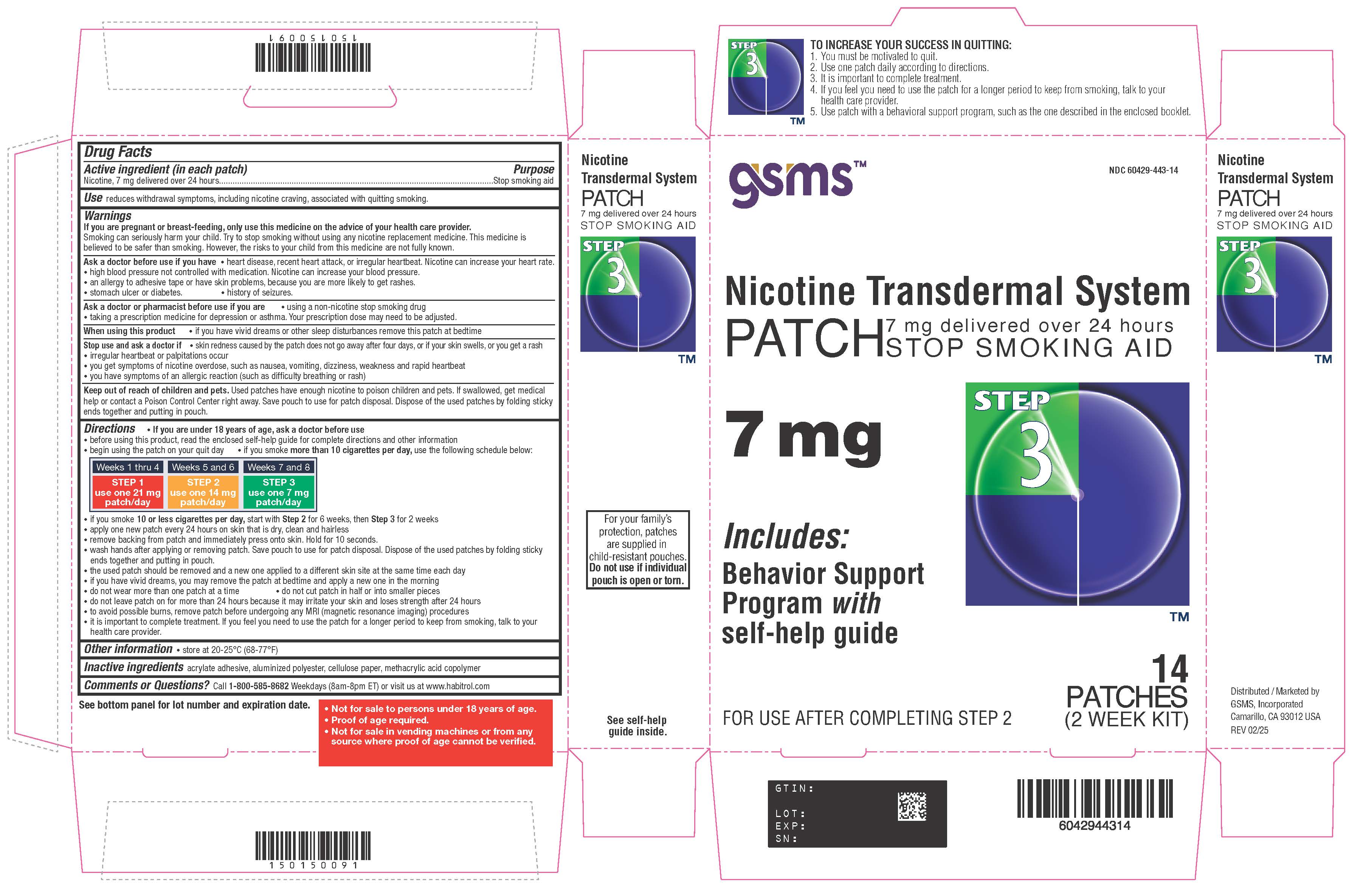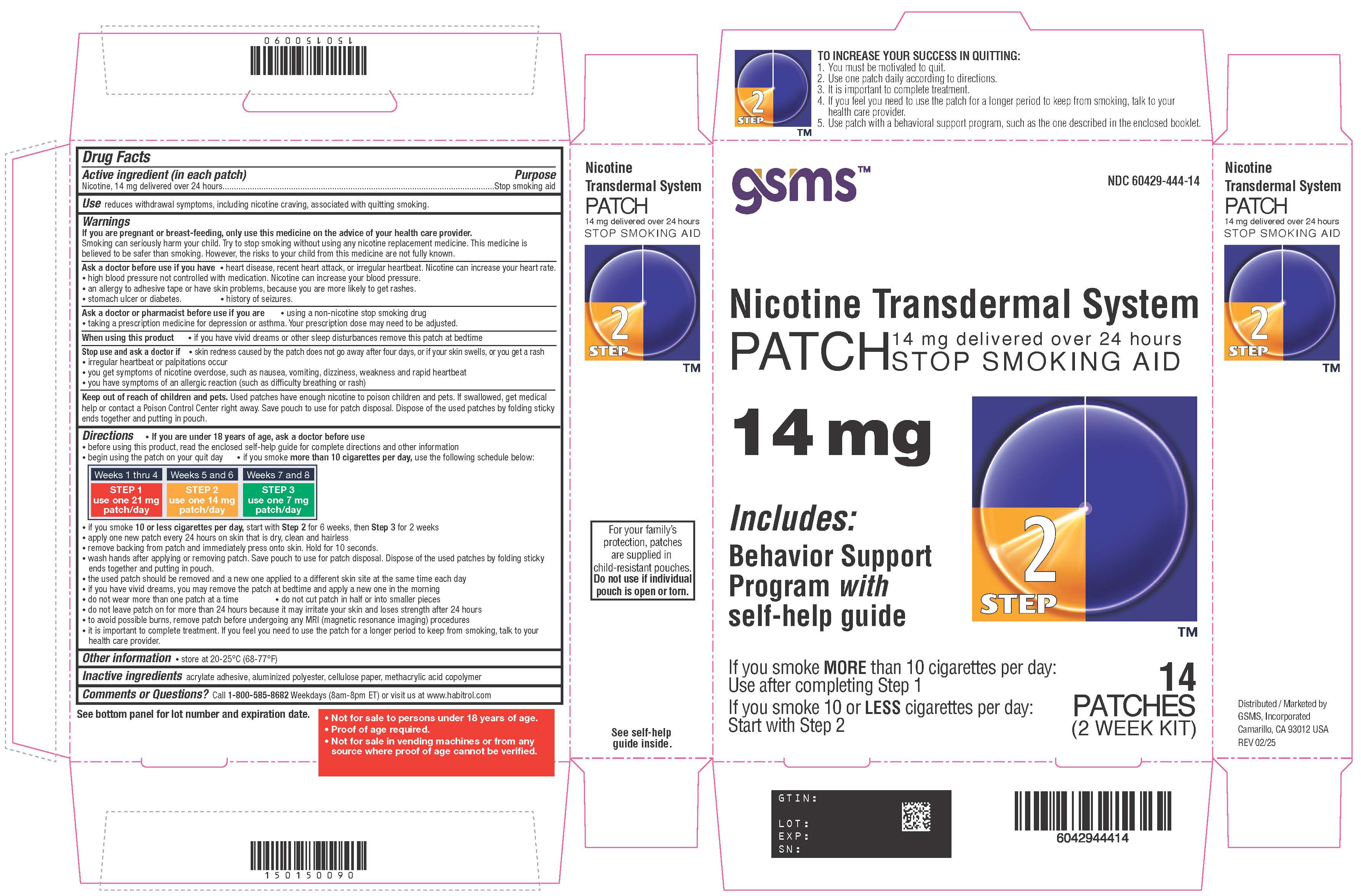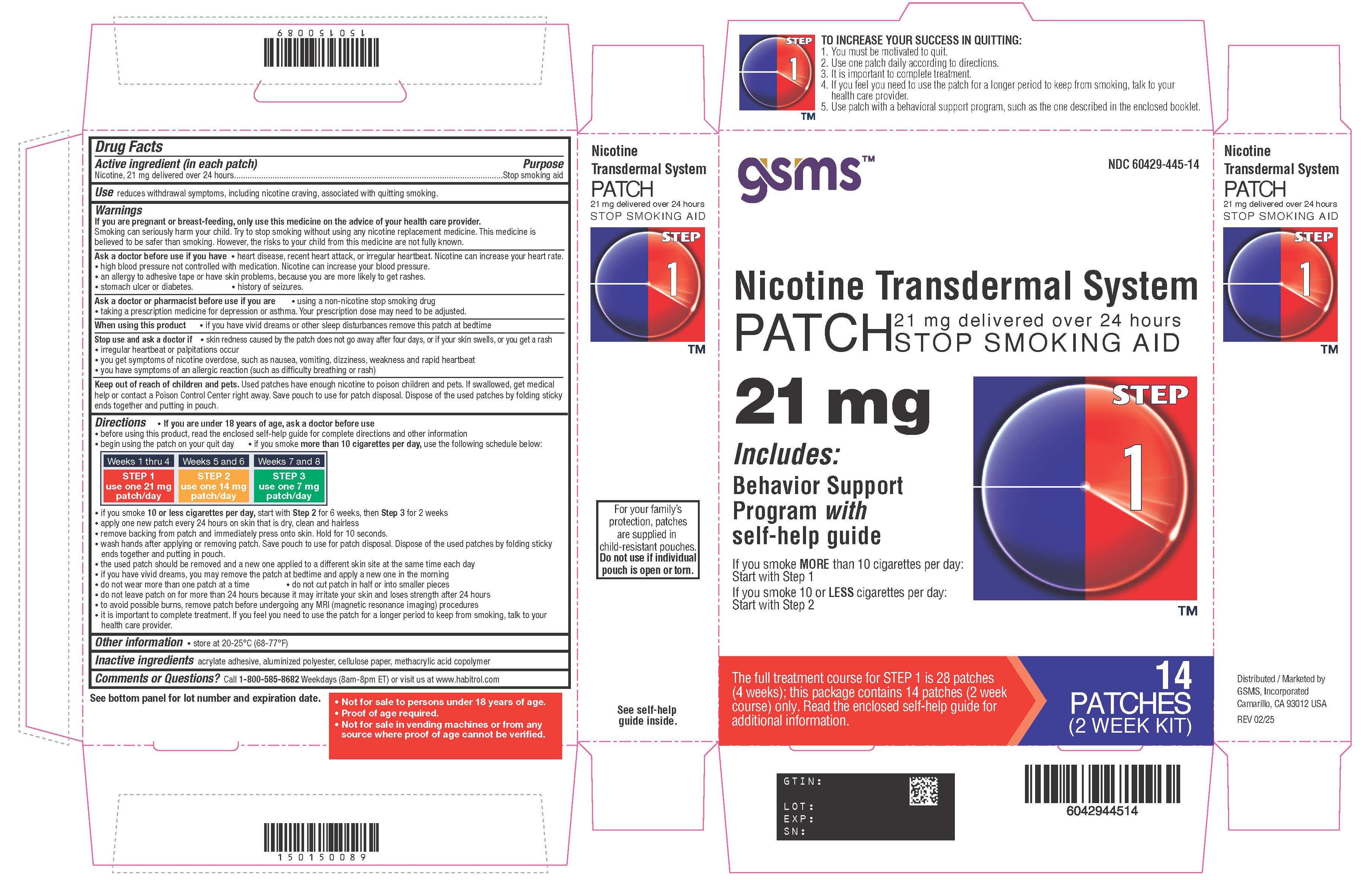 DRUG LABEL: Nicotine
NDC: 60429-445 | Form: PATCH, EXTENDED RELEASE
Manufacturer: Golden State Medical Supply, Inc.
Category: otc | Type: HUMAN OTC DRUG LABEL
Date: 20250417

ACTIVE INGREDIENTS: NICOTINE 21 mg/24 h
INACTIVE INGREDIENTS: METHACRYLIC ACID

NICOTINE PATCH
Drug Facts

Active ingredient Step 1 (in each patch)

Nicotine, 21 mg delivered over 24 hours

Active ingredient Step 2 (in each patch)

Nicotine, 14 mg delivered over 24 hours

Active ingredient Step 3 (in each patch)

Nicotine, 7 mg delivered over 24 hours

Purpose

Stop smoking aid

Use

reduces withdrawal symptoms, including nicotine craving, associated with quitting smoking

WARNINGS SECTION

If you are pregnant or breast-feeding, only use this medicine on the advice of your health care provider.

Smoking can seriously harm your child.

Try to stop smoking without using any nicotine replacement medicine.

This medicine is believed to be safer than smoking. However, the risks to your child from this medicine are not fully known.

Ask a doctor before use if you have

•heart disease, recent heart attack, or irregular heartbeat.

• Nicotine can increase your heart rate.high blood pressure not controlled with medication.

• Nicotine can increase your blood pressure.an allergy to adhesive tape or have skin problems, because you are more likely to get rashes.

• stomach ulcer or diabetes.history of seizures.

Ask a doctor or pharmacist before use if you are

•using a non-nicotine stop smoking drug

•taking a prescription medicine for depression or asthma. Your prescription dose may need to be adjusted.

When using this product

•if you have vivid dreams or other sleep disturbances remove this patch at bedtime•

Stop use and ask a doctor if

•skin redness caused by the patch does not go away after four days, or if your skin swells, or you get a rash

•irregular heartbeat or palpitations occur.

•you get symptoms of nicotine overdose, such as nausea, vomiting, dizziness, weakness and rapid heartbeat.

•you have symptoms of an allergic reaction (such as difficulty breathing or rash).

Keep out of reach of children and pets

•Used patches have enough nicotine to poison children and pets.

• If swallowed, get medical help or contact a Poison Control Center right away.

• Save pouch to use for patch disposal.

• Dispose of the used patches by folding sticky ends together and putting in pouch.

Directions

- if you are under 18 years of age, ask a doctor before use
- before using this product, read the enclosed self-help guide for complete directions and other information
- begin using the patch on your quit day
- if you smoke more than 10 cigarettes per day,use the following schedule below:

STEP 1 | STEP 2 | STEP 3
Use one 21 mg patch/day | Use one 14 mg patch/day | Use one 7 mg patch/day
Weeks 1-4 | Weeks 5-6 | Weeks 7-8

- if you smoke 10 or less cigarettes per day, start with Step 2for 6 weeks, then Step 3for 2 weeks
- apply one new patch every 24 hours on skin that is dry, clean and hairless
- remove backing from patch and immediately press onto skin. Hold for 10 seconds.
- wash hands after applying or removing patch. Save pouch to use for patch disposal. Dispose of the used patches by folding sticky ends together and putting in pouch.
- the used patch should be removed and a new one applied to a different skin site at the same time each day
- if you have vivid dreams, you may remove the patch at bedtime and apply a new one in the morning
- do not wear more than one patch at a time
- do not cut patch in half or into smaller pieces
- do not leave patch on for more than 24 hours because it may irritate your skin and loses strength after 24 hours
- to avoid possible burns, remove patch before undergoing any MRI (magnetic resonance imaging) procedures
- It is important to complete treatment. If you feel you need to use the patch for a longer period to keep from smoking, talk to your health care provider.

Other information

store at 20-25°C (68-77°F)

Inactive ingredients

acrylate adhesive, aluminized polyester, cellulose paper, methacrylic acid copolymer

Questions or comments?

call 1-800-585-8682

Weekdays (9am-8pm ET) or visit us at www.habitrol.com

TO INCREASE YOUR SUCCESS IN QUITTING:

1. You must be motivated to quit.

2. Use one patch daily according to directions.

3. It is important to complete treatment.

4. If you feel you need to use the patch for a longer period to keep from smoking, talk to your health care provider.

5. Use patch with a behavioural support program, such as the one described in the enclosed booklet.

For your family's protection, patches are supplied in child-resistant pouches. Do not use if individual pouch is open or torn.

- Not for sale to persons under 18 years of age.
- Proof of age required.
- Not for sale in vending machines or from any source where proof of age cannot be verified.

Marketed by:

GSMS, Inc.

Camarillo, CA 93012 USA

Principal Display Panel

Nicotine Transdermal System PATCH

21 mg delivered over 24 hours

STOP SMOKING AID

Includes: Behavior Support Programwithself-help guide

STEP 1

IF YOU SMOKE MORETHAN 10 CIGARETTES PER DAY: START WITH STEP 1

IF YOU SMOKE 10 OR LESSCIGARETTES PER DAY: START WITH STEP 2

Principal Display Panel

Nicotine Transdermal System PATCH

14 mg delivered over 24 hours

STOP SMOKING AID

Includes: Behavior Support Programwithself-help guide

STEP 2

IF YOU SMOKE MORETHAN 10 CIGARETTES PER DAY: USE AFTER COMPLETING STEP 1

IF YOU SMOKE 10 OR LESSCIGARETTES PER DAY: START WITH STEP 2

Principal Display Panel

Nicotine Transdermal System PATCH

7 mg delivered over 24 hours

STOP SMOKING AID

Includes: Behavior Support Programwithself-help guide

STEP 3

FOR USE AFTER COMPLETING STEP 2